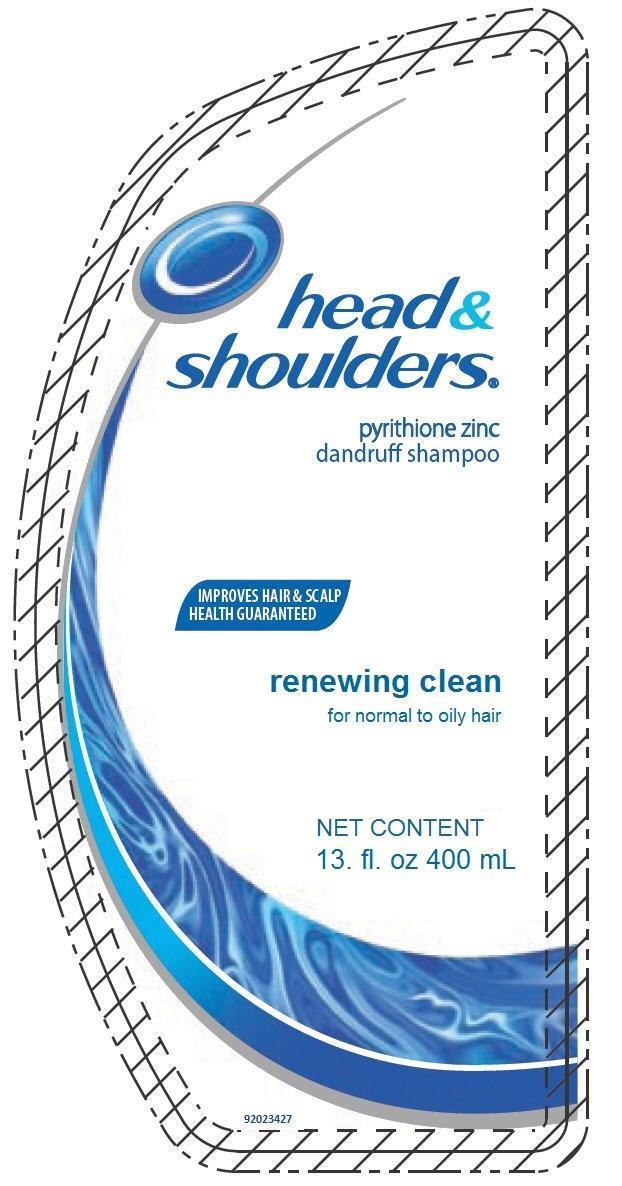 DRUG LABEL: HEAD AND SHOULDERS
NDC: 69772-139 | Form: LOTION/SHAMPOO
Manufacturer: Teresa Cecena DBA Genesis
Category: otc | Type: HUMAN OTC DRUG LABEL
Date: 20170418

ACTIVE INGREDIENTS: PYRITHIONE ZINC 0.01 g/1 mL
INACTIVE INGREDIENTS: CYCLOHEXYL CINNAMATE; METHYLCHLOROISOTHIAZOLINONE; D&C RED NO. 33; SODIUM CHLORIDE; SODIUM XYLENESULFONATE; COCAMIDOPROPYL BETAINE; SODIUM BENZOATE; DIMETHICONE; ZINC CARBONATE; C.I. ACID BLUE 324; WATER; SODIUM LAURYL SULFATE; SODIUM LAURETH SULFATE; GLYCOL DISTEARATE; GUAR HYDROXYPROPYLTRIMONIUM CHLORIDE (1.7 SUBSTITUENTS PER SACCHARIDE); HYDROCHLORIC ACID; MAGNESIUM CARBONATE HYDROXIDE; METHYLISOTHIAZOLINONE

WARNINGS

WARNININGS

FOR EXTERNAL USE ONLY.

WHEN USING THIS PRODUCT

- Avoid contact with eyes. If contact occurs, rinse eyes thoroughly with water.

Stop use and ask a doctor if

condition worsens or does not improve after regular use of this product as directed.

DIRECTIONS

- for maximum dandruff control, use every time you shampoo.
- wet hair, message onto scalp, rinse, repeat if desired.
- for best results use at least twice a week or as directed by a doctor.

ACTIVE INGREDIENT

PYRITHIONE ZINC 1%

INACTIVE INGREDIENT

Water,sodium laureth sulfate, sodium lauryl sulfate, cocamide mea, zinc carbonate, glycol distearate, dimethicone, fragance, guarhydroxypropyltrimonium chloride, magnesium sulfate, sodium benzoate, magnesium carbonate hydroxide, ammonium laureth sulfate, sodium chloride, methylchloroisothiazolinone,methylisothiazolinone, sodium xylenesulfonate, blue 1, D&C red 33.

KEEP OUT OF REACH OF CHILDREN

KEEP THIS AND ALL DRUGS OUT OF REACH OF CHILDREN

PURPOSE

Anti-drandruff

DOSAGE AND ADMINISTRATION

FOR EXTERNAL USE ONLY

FOR BEST RESULTS USE A LEAST TWICE A WEEK OR AS DIRECTED BY A DOCTOR